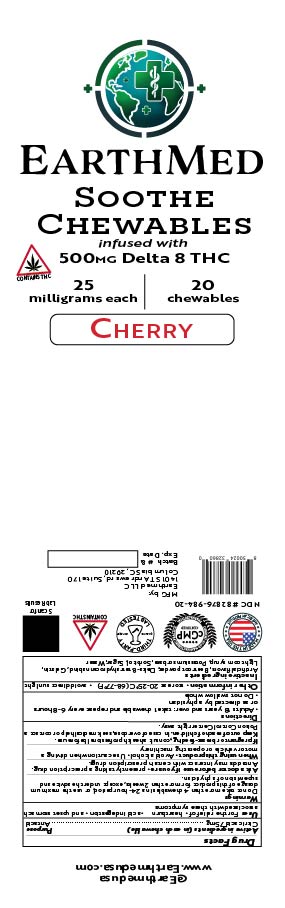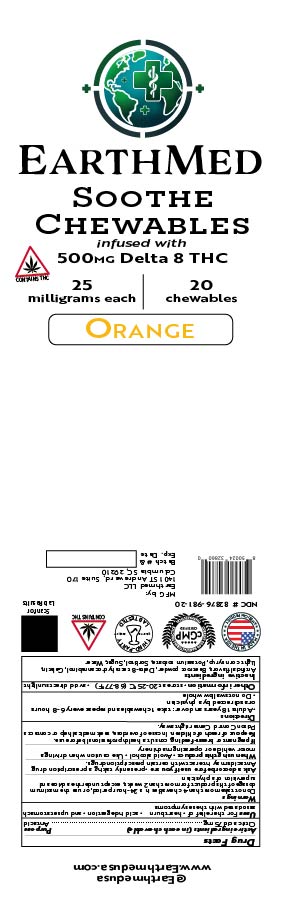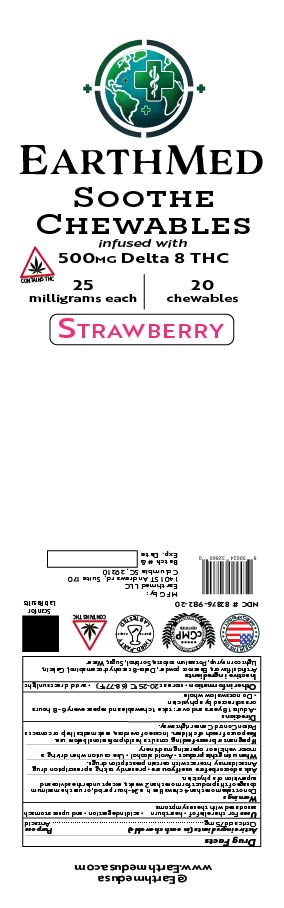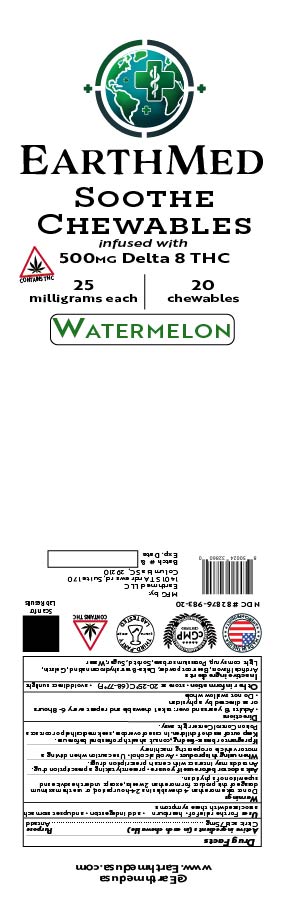 DRUG LABEL: Earthmed Soothe Chewable Cherry
NDC: 82876-984 | Form: CHEWABLE GEL
Manufacturer: Earthmed LLC
Category: otc | Type: HUMAN OTC DRUG LABEL
Date: 20251114

ACTIVE INGREDIENTS: CITRIC ACID MONOHYDRATE 1.5 g/108.27 g
INACTIVE INGREDIENTS: SUCROSE 34.9 g/108.27 g; SORBITOL 2.9 g/108.27 g; GELATIN 6.78 g/108.27 g; .DELTA.8-TETRAHYDROCANNABINOL, (6AS-CIS)- 0.575 g/108.27 g; POTASSIUM SORBATE 0.1 g/108.27 g; BETA VULGARIS ROOT FRUCTOOLIGOSACCHARIDES 0.12 g/108.27 g; CORN SYRUP 33.9 g/108.27 g; WATER 27.75 g/108.27 g

Earthmed Soothe Chewables

Active ingredients (in each chewable)

Citric Acid 75mg

Purpose

Antacid

Uses

For the relief of Heartburn, acid indigestion, and upset stomach associated with these symptoms.

Warnings

Do not take more than 4 chewables in a 24-hour period, or use the maximum dosage of this product for more than 2 weeks except under the advice and supervision of a physician

Do not use

Do not take more than 4 chewables in a 24-hour period, or use the maximum dosage of this product for more than 2 weeks except under the advice and supervision of a physician

Ask a doctor before use if you are

Presently taking a prescription drug, Antacids may interact with certain prescription drugs

Stop using and ask a doctor if

Presently taking a prescription drug, Antacids may interact with certain prescription drugs

If pregnant or breast-feeding

consult a health professional before use

Keep out of reach of children

In case of overdose seek medical help or contact a poison control center right away

Keep out of reach of children

In case of overdose, seek medical help or contact a poison control center right away

Directions

Adults 18 years of age and over: take up 1 chewable and repeat every 6 to 8 hours or as directed by a physician

Do not swallow whole

Other information

Store at 68-77 degrees F

Avoid direct sunlight

Inactive ingredients

Artificial flavors, Gelatin, Delta 8 Tetrahydrocannabinol, Light corn syrup, Potassium Sorbate, Sorbitol, Beta Vulgaris powder, Sugar, Water.